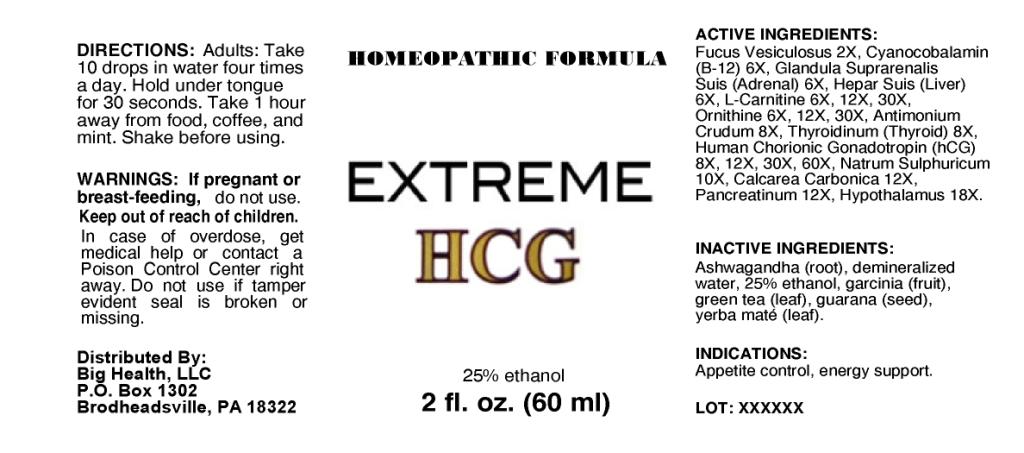 DRUG LABEL: Extreme HCG
NDC: 57520-0182 | Form: LIQUID
Manufacturer: Apotheca Company
Category: homeopathic | Type: HUMAN OTC DRUG LABEL
Date: 20101116

ACTIVE INGREDIENTS: FUCUS VESICULOSUS 2 [hp_X]/1 mL; CYANOCOBALAMIN 6 [hp_X]/1 mL; SUS SCROFA ADRENAL GLAND 6 [hp_X]/1 mL; PORK LIVER 6 [hp_X]/1 mL; LEVOCARNITINE 30 [hp_X]/1 mL; ORNITHINE 30 [hp_X]/1 mL; ANTIMONY TRISULFIDE 8 [hp_X]/1 mL; HUMAN CHORIONIC GONADOTROPIN 60 [hp_X]/1 mL; SUS SCROFA THYROID 8 [hp_X]/1 mL; SODIUM SULFATE 10 [hp_X]/1 mL; OYSTER SHELL CALCIUM CARBONATE, CRUDE 12 [hp_X]/1 mL; SUS SCROFA HYPOTHALAMUS 18 [hp_X]/1 mL; PANCRELIPASE 12 [hp_X]/1 mL
INACTIVE INGREDIENTS: WATER; ALCOHOL; GREEN TEA LEAF; ILEX PARAGUARIENSIS LEAF; GUARANA; WITHANIA SOMNIFERA ROOT; HYDROXYCITRIC ACID

Extreme HCG

ACTIVE INGREDIENT

ACTIVE INGREDIENTS: Fucus vesiculosus 2X, Cyanocobalamin (B-12) 6X, Glandula Suprarenalis suis (adrenal) 6X, Hepar suis (liver) 6X, L-carnitine 6X, 12X, 30X, Ornithine 6X, 12X, 30X, Antimonium crudum 8X, Human chorionic gonadotropin (hCG) 8X, 12X, 30X, 60X, Thyroidinum (thyroid) 8X, Natrum sulphuricum 10X, Calcarea carbonica 12X, Pancreatinum 12X, Hypothalamus 18X.

PURPOSE

INDICATIONS: Appetite control, energy support.

WARNINGS

WARNINGS: If pregnant or breast-feeding, do not use.

Keep out of reach of children. In case of overdose, get medical help or contact a Poison Control Center right away.

Do not use if tamper evident seal is broken or missing.

DOSAGE AND ADMINISTRATION

DIRECTIONS: Adults: Take 10 drops in water four times a day. Hold under tongue for 30 seconds. Take 1 hour away from food, coffee, and mint. Shake before using.

INACTIVE INGREDIENT

INACTIVE INGREDIENTS: Demineralized water, 25% Ethanol, Green tea (leaf), Yerba mate (leaf), Guarana (seed), Ashwagandha (root), Garcinia (fruit).

KEEP OUT OF REACH OF CHILDREN. In case of overdose, get medical help or contact a Poison Control Center right away.

INDICATIONS: Appetite control, energy support.

QUESTIONS

Distributed By:

Big Health, LLC

P.O.Box 1302

Brodheadsville, PA 18322

PACKAGE LABEL

HOMEOPATHIC FORMULA

EXTREME HCG

2 fl. oz. (60 ml)